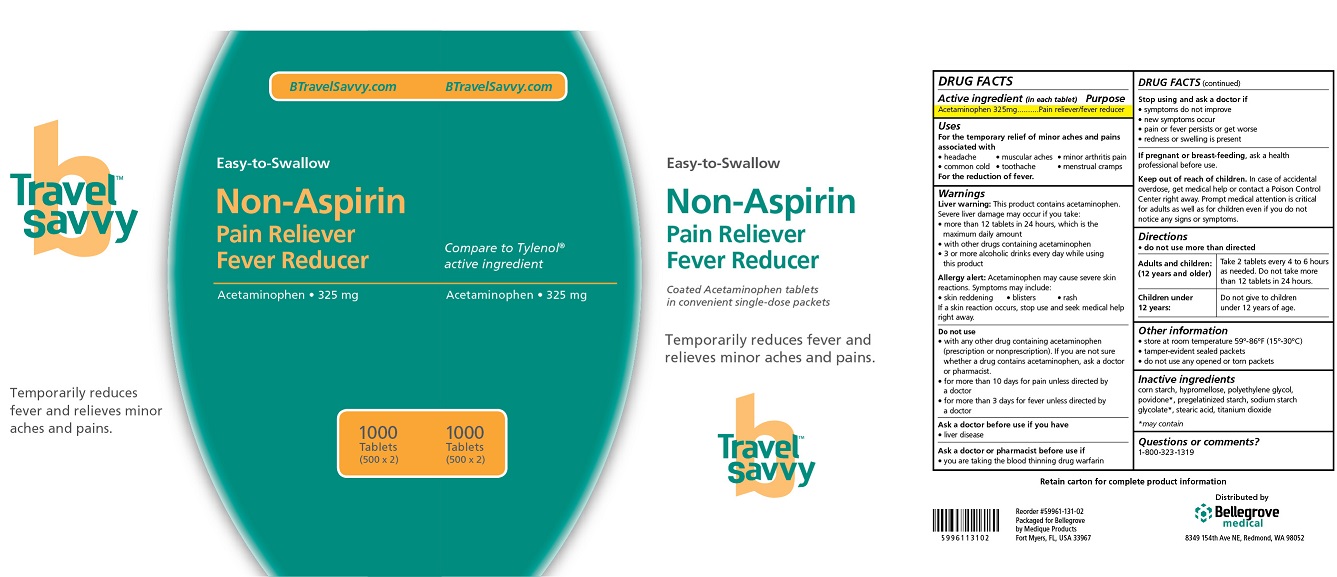 DRUG LABEL: Travel Savvy Non-Aspirin
NDC: 59961-151 | Form: TABLET, COATED
Manufacturer: Bellegrove Medical Supply, Inc.
Category: otc | Type: HUMAN OTC DRUG LABEL
Date: 20250909

ACTIVE INGREDIENTS: ACETAMINOPHEN 325 mg/1 1
INACTIVE INGREDIENTS: STARCH, CORN; STEARIC ACID; TITANIUM DIOXIDE; HYPROMELLOSES; POLYETHYLENE GLYCOL, UNSPECIFIED; POVIDONE; SODIUM STARCH GLYCOLATE TYPE A POTATO

Travel Savvy Non-Aspirin

Active ingredient

Acetaminophen 325 mg

Purpose

Pain reliever/fever reducer

Uses

For the temporary relief of minor aches and pains associated with

- headache
- common cold
- muscular aches
- toothache
- minor arthritis pain
- menstrual cramps

For the reduction of fever.

Warnings

Liver warning:

This product contains acetaminophen. Severe liver damage may occur if you take:

- more than 12 tablets in 24 hours, which is the maximum daily amount
- with other drugs containing acetaminophen
- 3 or more alcoholic drinks every day while using this product

Allergy alert:

Acetaminophen may cause severe skin reactions. Symptoms may include:

- skin reddening
- blisters
- rash

If a skin reaction occurs, stop use and seek medical help right away.

Do not use

- with any other drug containing acetaminophen (prescription or nonprescription).
  If you are not sure whether a drug contains acetaminophen, ask a doctor or pharmacist.
- for more than 10 days for pain unless directed by a doctor
- for more than 3 days for fever unless directed by a doctor

Ask a doctor before use if you have

- liver disease

Ask a doctor or pharmacist before use if

- you are taking the blood thinning drug warfarin

Stop using and ask a doctor if

- symptoms do not improve
- new symptoms occur
- pain or fever persists or gets worse
- redness or swelling is present

If pregnant or breast-feeding,

ask a health professional before use.

Keep out of reach of children.

In case of accidental overdose, get medical help or contact a Poison Control Center right away. Prompt medical attention is critical for adults as well as for children even if you do not notice any signs or symptoms.

Directions

- do not use more than directed

Adults and children: (12 years and older)

Take 2 tablets every 4 to 6 hours as needed. Do not take more than 12 tablets in 24 hours.

Children under 12 years:

Do not give to children under 12 years of age.

Other information

- store at room temperature 59°-86°F (15°-30°C)
- tamper-evident sealed packets
- do not use any opened or torn packets

Inactive ingredients

corn starch, hypromellose, maltodextrin*, microcrystalline cellulose*, polyethylene glycol, povidone*, pregelatinized starch*, sodium starch glycolate*, stearic acid, titanium dioxide*

* may contain

Questions or comments?

1-800-323-1319

Travel Savvy Non-Aspirin Label

BTravelSavvy.com

Travel Savvy

Non-Aspirin

Pain Reliever

Fever Reducer

Temporarily reduces fever

and relieves minor aches

and pains.

1000

Tablets

(500 x 2)